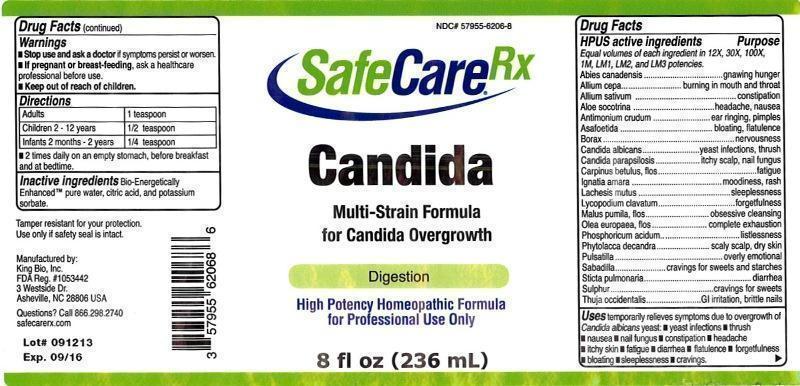 DRUG LABEL: Candida
NDC: 57955-6206 | Form: LIQUID
Manufacturer: King Bio Inc.
Category: homeopathic | Type: HUMAN OTC DRUG LABEL
Date: 20131011

ACTIVE INGREDIENTS: TSUGA CANADENSIS FLOWER BUD 12 [hp_X]/236 mL; ONION 12 [hp_X]/236 mL; GARLIC 12 [hp_X]/236 mL; ALOE 12 [hp_X]/236 mL; ANTIMONY TRISULFIDE 12 [hp_X]/236 mL; ASAFETIDA 12 [hp_X]/236 mL; SODIUM BORATE 12 [hp_X]/236 mL; CANDIDA ALBICANS 12 [hp_X]/236 mL; CANDIDA PARAPSILOSIS 12 [hp_X]/236 mL; CARPINUS BETULUS FLOWERING TOP 12 [hp_X]/236 mL; STRYCHNOS IGNATII SEED 12 [hp_X]/236 mL; LACHESIS MUTA VENOM 12 [hp_X]/236 mL; LYCOPODIUM CLAVATUM SPORE 12 [hp_X]/236 mL; MALUS DOMESTICA FLOWER 12 [hp_X]/236 mL; OLEA EUROPAEA FLOWER 12 [hp_X]/236 mL; PHOSPHORIC ACID 12 [hp_X]/236 mL; PHYTOLACCA AMERICANA ROOT 12 [hp_X]/236 mL; PULSATILLA VULGARIS 12 [hp_X]/236 mL; SCHOENOCAULON OFFICINALE SEED 12 [hp_X]/236 mL; LOBARIA PULMONARIA 12 [hp_X]/236 mL; SULFUR 12 [hp_X]/236 mL; THUJA OCCIDENTALIS LEAFY TWIG 12 [hp_X]/236 mL
INACTIVE INGREDIENTS: WATER; CITRIC ACID MONOHYDRATE; POTASSIUM SORBATE

Candida™

Drug Facts

____________________________________________________________________________________________________________

HPUS active ingredients: Abies canadensis, Allium cepa, Allium sativum, Aloe socotrina, Antimonium crudum, Asafoetida, Borax, Candida albicans, Candida parapsilosis, Carpinus betulus, flos, Ignatia amara, Lachesis mutus, Lycopodium clavatum, Malus pumila, flos, Olea europaea, flos, Phosphoricum acidum, Phytolacca decandra, Pulsatilla, Sabadilla, Sticta pulmonaria, Sulphur, Thuja occidentalis.

INDICATIONS AND USAGE

Uses temporarily relieves symptoms due to overgrowth of Candida abicans yeast:

- yeast infections
- thrush
- nausea
- nail fungus
- constipation
- headache
- itchy skin
- fatigue
- diarrhea
- flatulence
- forgetfulness
- bloating
- sleeplessness
- cravings

Warnings

- Stop use and ask a docter if symptoms persist or worsen.
- If pregnant or breast-feeding, ask a healthcare professional before use.

- Keep out of reach of children.

Directions:

Adults 1 teaspoon

Children 2-12 years ½ teaspoon

Infants 2 months-2 years ¼ teaspoon

- 2 times daily on an empty stomach, before breakfast and at bedtime.

INACTIVE INGREDIENT

Inactive Ingredients: Bio-Energetically Enhanced™ pure water, citric acid and potassium sorbate.

OTHER SAFETY INFORMATION

Tamper resistant for your protection. Use only if safety seal is intact.

Drug Facts

__________________________________________________________________________________________________________________

HPUS active ingredients Purpose

Equal volumes of each ingredient in 12X, 30X, 100X, 1M, LM1, LM2 and LM3 potencies.

Abies canadensis.........................................................gnawing hunger

Allium cepa.................................................................burning in mouth and throat

Allium sativum............................................................constipation

Aloe socotrina..............................................................headache, nausea

Antimonium crudum.....................................................ear ringing, pimples

Asafoetida...................................................................bloating, flatulence

Borax..........................................................................nervousness

Candida albicans.........................................................yeast infection, thrush

Candida parapsilosis.....................................................itchy scalp, nail fungus

Carpinus betulus, flos...................................................fatigue

Ignatia amara..............................................................moodiness, rash

Lachesis mutus............................................................sleeplessness

Lycopodium clavatum....................................................forgetfulness

Malus pumila, flos........................................................obsessive cleansing

Olea europaea, flos.......................................................complete exhaustion

Phosphoricum acidum....................................................listlessness

Phytolacca decandra......................................................scaly scalp, dry skin

Pulsatilla......................................................................overly emotional

Sabadilla......................................................................craving for sweets and starches

Sticta pulmonaria..........................................................diarrhea

Sulphur........................................................................cravings for sweets

Thuja occidentalis..........................................................GI irritation, brittle nails